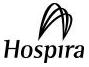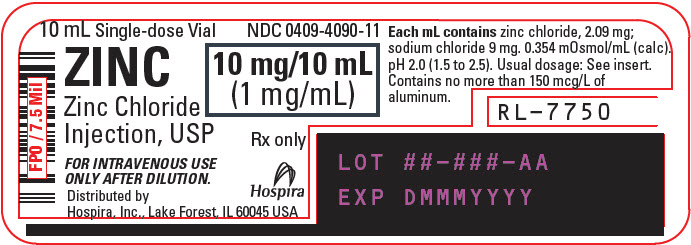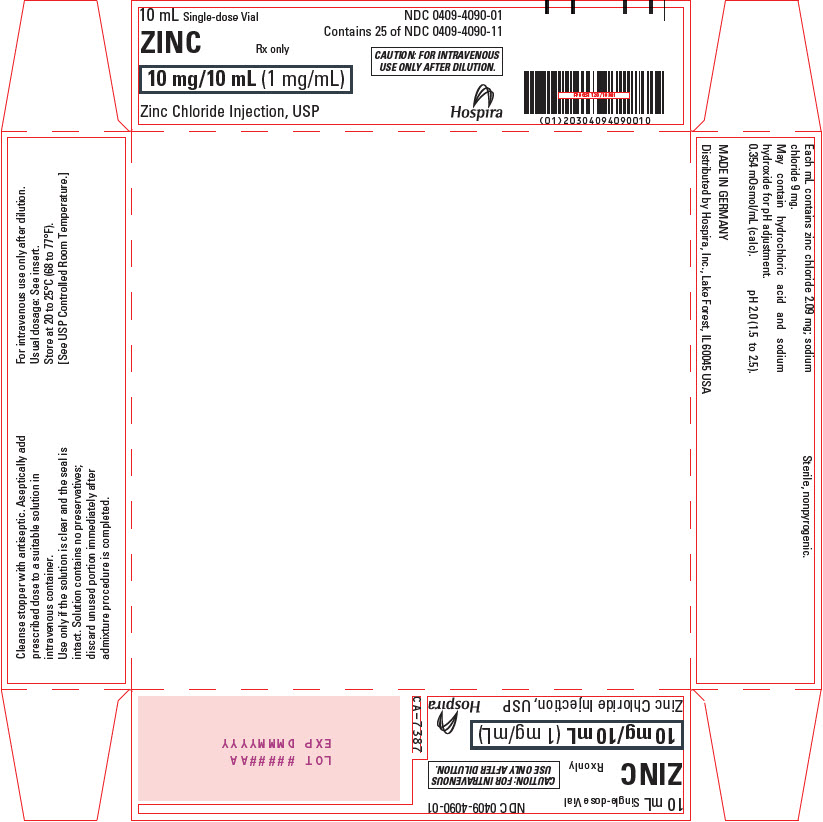 DRUG LABEL: ZINC
NDC: 0409-4090 | Form: INJECTION, SOLUTION
Manufacturer: Hospira, Inc.
Category: prescription | Type: HUMAN PRESCRIPTION DRUG LABEL
Date: 20241101

ACTIVE INGREDIENTS: ZINC CHLORIDE 1 mg/1 mL
INACTIVE INGREDIENTS: SODIUM CHLORIDE 9 mg/1 mL; HYDROCHLORIC ACID; SODIUM HYDROXIDE

ZINC
1 mg/mL
Zinc Chloride Injection, USP

FOR I.V. USE ONLY AFTER DILUTION

Plastic Vial

Rx Only

DESCRIPTION

Zinc 1 mg/mL (Zinc Chloride Injection, USP) is a sterile, nonpyrogenic solution intended for use as an additive to intravenous solutions for total parenteral nutrition. Each mL of solution contains 2.09 mg zinc chloride and 9 mg sodium chloride. The solution contains no bacteriostat, antimicrobial agent or added buffer. The pH is 2.0 (1.5 to 2.5); product may contain hydrochloric acid and sodium hydroxide for pH adjustment. The osmolarity is 0.354 mOsmoL/mL (calc.).

Zinc Chloride, USP is chemically designated ZnCl2, a white crystalline compound freely soluble in water.

Sodium Chloride, USP is chemically designated NaCl, a white crystalline compound freely soluble in water.

The semi-rigid vial is fabricated from a specially formulated polyolefin. It is a copolymer of ethylene and propylene. The safety of the plastic has been confirmed by tests in animals according to USP biological standards for plastic containers. The small amount of water vapor that can pass through the plastic container wall will not significantly alter the drug concentration.

CLINICAL PHARMACOLOGY

Zinc is an essential nutritional requirement and serves as a cofactor for more than 70 different enzymes including carbonic anhydrase, alkaline phosphatase, lactic dehydrogenase, and both RNA and DNA polymerase. Zinc facilitates wound healing, helps maintain normal growth rates, normal skin hydration, and the senses of taste and smell.

Zinc resides in muscle, bone, skin, kidney, liver, pancreas, retina, prostate and particularly in the red and white blood cells. Zinc binds to plasma albumin, α2-macroglobulin, and some plasma amino acids including histidine, cysteine, threonine, glycine, and asparagine. Ingested zinc is excreted mainly in the stool (approximately 90%), and to a lesser extent in the urine and in perspiration.

Providing zinc helps prevent development of deficiency symptoms such as: Parakeratosis, hypogeusia, anorexia, dysosmia, geophagia, hypogonadism, growth retardation and hepatosplenomegaly.

The initial manifestations of hypozincemia in total parenteral nutrition are diarrhea, apathy and depression. At plasma levels below 20 mcg zinc/100 mL dermatitis followed by alopecia has been reported for total parenteral nutrition patients. Normal zinc plasma levels are 100 ± 12 mcg/100 mL.

INDICATIONS AND USAGE

Zinc 1 mg/mL (Zinc Chloride Injection, USP) is indicated for use as a supplement to intravenous solutions given for total parenteral nutrition. Administration helps to maintain zinc serum levels and to prevent depletion of endogenous stores, and subsequent deficiency symptoms.

CONTRAINDICATIONS

None known.

WARNINGS

Direct intramuscular or intravenous injection of Zinc 1 mg/mL (Zinc Chloride Injection, USP) is contraindicated as the acidic pH of the solution (2) may cause considerable tissue irritation.

Severe kidney disease may make it necessary to reduce or omit chromium and zinc doses because these elements are primarily eliminated in the urine.

Copper Deficiency

Several post-marketing cases have reported that zinc products taken over extended periods of time (i.e., months to years) may result in copper deficiency. The cases reported the following complications of copper deficiency: anemia, granulocytopenia, leukopenia, neutropenia, pancytopenia, thrombocytopenia, and myeloneuropathy.

If a patient develops signs and/or symptoms of copper deficiency during treatment with zinc chloride, interrupt zinc treatment and check zinc and copper levels. Consider supplemental copper administration to treat copper deficiency and monitor zinc levels.

Aluminum Toxicity

This product contains aluminum that may be toxic. Aluminum may reach toxic levels with prolonged parenteral administration if kidney function is impaired. Premature neonates are particularly at risk because their kidneys are immature, and they require large amounts of calcium and phosphate solutions, which contain aluminum.

Research indicates that patients with impaired kidney function, including premature neonates, who receive parenteral levels of aluminum at greater than 4 to 5 mcg/kg/day accumulate aluminum at levels associated with central nervous system and bone toxicity. Tissue loading may occur at even lower rates of administration.

PRECAUTIONS

General

Use only if the solution is clear and the seal is intact.

Zinc 1 mg/mL (Zinc Chloride Injection, USP) should only be used in conjunction with a pharmacy directed admixture program using aseptic technique in a laminar flow environment; it should be used promptly and in a single operation without any repeated penetrations. Solution contains no preservatives; discard unused portion immediately after admixture procedure is completed.

Zinc should not be given undiluted by direct injection into a peripheral vein because of the likelihood of infusion phlebitis and the potential for increased excretory loss of zinc from a bolus injection. Administration of zinc in the absence of copper may cause a decrease in serum copper levels.

Laboratory Tests

Periodic determinations of serum copper as well as zinc are suggested as a guideline for subsequent zinc administration.

Carcinogenesis, Mutagenesis, and Impairment of Fertility

Long-term animal studies to evaluate the carcinogenic potential of Zinc 1 mg/mL (Zinc Chloride Injection, USP) have not been performed, nor have studies been done to assess mutagenesis or impairment of fertility.

Nursing Mothers

It is not known whether this drug is excreted in human milk. Because many drugs are excreted in human milk, caution should be exercised when Zinc 1 mg/mL (Zinc Chloride Injection, USP) is administered to a nursing woman.

Pediatric Use

See DOSAGE and ADMINISTRATION section.

Pregnancy

Animal reproduction studies have not been conducted with zinc chloride. It is also not known whether zinc chloride can cause fetal harm when administered to a pregnant woman or can affect reproduction capacity. Zinc chloride should be given to a pregnant woman only if clearly needed.

Geriatric Use

An evaluation of current literature revealed no clinical experience identifying differences in response between elderly and younger patients. In general, dose selection for an elderly patient should be cautious, usually starting at the low end of the dosing range, reflecting the greater frequency of decreased hepatic, renal, or cardiac function, and of concomitant disease or other drug therapy.

ADVERSE REACTIONS

None known.

OVERDOSAGE

Single intravenous doses of 1 to 2 mg zinc/kg body weight have been given to adult leukemic patients without toxic manifestations. However, acute toxicity was reported in an adult when 10 mg zinc was infused over a period of one hour on each of four consecutive days. Profuse sweating, decreased level of consciousness, blurred vision, tachycardia (140/min), and marked hypothermia (94.2° F) on the fourth day were accompanied by a serum zinc concentration of 207 mcg/dl. Symptoms abated within three hours.

Hyperamylasemia may be a sign of impending zinc overdosage; patients receiving an inadvertent overdose (25 mg zinc/liter of total parenteral nutrition solution, equivalent to 50 to 70 mg zinc/day) developed hyperamylasemia (557 to 1850 Klein units; normal: 130 to 310).

Death resulted from an overdosage in which 1683 mg zinc was delivered intravenously over the course of 60 hours to a 72-year-old patient.

Symptoms of zinc toxicity included hypotension (80/40 mm Hg), pulmonary edema, diarrhea, vomiting, jaundice, and oliguria, with a serum zinc level of 4184 mcg/dl.

Calcium supplements may confer a protective effect against zinc toxicity.

DOSAGE AND ADMINISTRATION

Zinc 1 mg/mL (Zinc Chloride Injection, USP) contains 1 mg zinc/mL and is administered intravenously only after dilution. The additive should be diluted prior to administration in a volume of fluid not less than 100 mL. For the metabolically stable adult receiving total parenteral nutrition, the suggested intravenous dosage is 2.5 to 4 mg zinc/day (2.5 to 4 mL/day). An additional 2 mg zinc/day (2 mL/day) is suggested for acute catabolic states. For the stable adult with fluid loss from the small bowel, an additional 12.2 mg zinc/liter of small bowel fluid lost (12.2 mL/liter of small bowel fluid lost), or an additional 17.1 mg zinc/kg of stool or ileostomy output (17.1 mL/kg of stool or ileostomy output) is recommended. Frequent monitoring of zinc blood levels is suggested for patients receiving more than the usual maintenance dosage level of zinc.

For full term infants and children up to 5 years of age, 100 mcg zinc/kg/day (0.1 mL/kg/day) is recommended. For premature infants (birth weight less than 1500 g) up to 3 kg in body weight, 300 mcg zinc/kg/day (0.3 mL/kg/day) is suggested.

Parenteral drug products should be inspected visually for particulate matter and discoloration prior to administration, whenever solution and container permit (See PRECAUTIONS).

HOW SUPPLIED

Zinc 1 mg/mL (Zinc Chloride Injection, USP) is supplied in 10 mL single-dose plastic vials.

Unit of Sale | Concentration | Each
NDC 0409-4090-01 | 10 mg/10 mL | NDC 0409-4090-11
Tray of 25 single-dose vials | (1 mg/mL) | 10 mg single-dose vial

Store at 20°C to 25°C (68°F to 77°F). [See USP Controlled Room Temperature.]

Distributed by Hospira, Inc., Lake Forest, IL 60045 USA

LAB-1069-4.0

Revised: 8/2024

PRINCIPAL DISPLAY PANEL - 10 mL Vial Label

10 mL Single-dose Vial
NDC 0409-4090-11

ZINC
Zinc Chloride
Injection, USP

10 mg/10 mL
(1 mg/mL)

Rx only

FOR INTRAVENOUS USE
ONLY AFTER DILUTION.

Hospira

Distributed by
Hospira, Inc., Lake Forest, IL 60045 USA

PRINCIPAL DISPLAY PANEL - 10 mL Vial Tray

10 mL Single-dose Vial
NDC 0409-4090-01
Contains 25 of NDC 0409-4090-11

ZINC
Rx only

10 mg/10 mL (1 mg/mL)

CAUTION: FOR INTRAVENOUS
USE ONLY AFTER DILUTION.

Zinc Chloride Injection, USP
Hospira